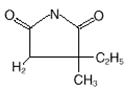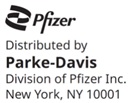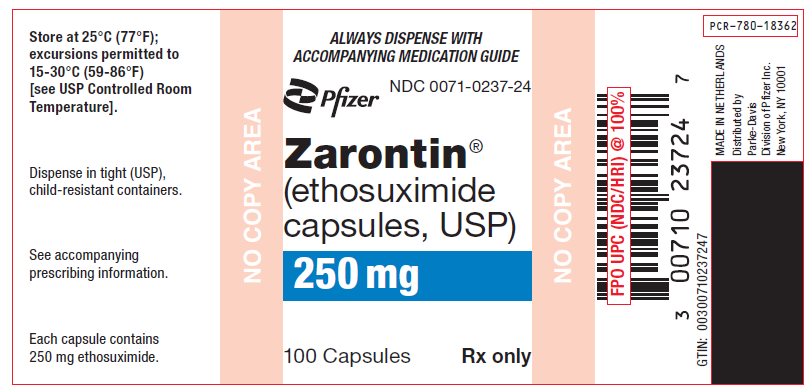 DRUG LABEL: Zarontin
NDC: 0071-0237 | Form: CAPSULE
Manufacturer: Parke-Davis Div of Pfizer Inc
Category: prescription | Type: HUMAN PRESCRIPTION DRUG LABEL
Date: 20240715

ACTIVE INGREDIENTS: ETHOSUXIMIDE 250 mg/1 1
INACTIVE INGREDIENTS: POLYETHYLENE GLYCOL 400; D&C YELLOW NO. 10; FD&C RED NO. 3; GELATIN, UNSPECIFIED; GLYCERIN; SORBITOL

Zarontin®
(Ethosuximide Capsules, USP)

DESCRIPTION

Zarontin (ethosuximide) is an anticonvulsant succinimide, chemically designated as alpha-ethyl-alpha-methyl-succinimide, with the following structural formula:

Each Zarontin capsule contains 250 mg ethosuximide, USP. Also contains: polyethylene glycol 400, NF. The capsule contains D&C yellow No. 10; FD&C red No. 3; gelatin, NF; glycerin, USP; and sorbitol.

CLINICAL PHARMACOLOGY

Ethosuximide suppresses the paroxysmal three cycle per second spike and wave activity associated with lapses of consciousness which is common in absence (petit mal) seizures. The frequency of epileptiform attacks is reduced, apparently by depression of the motor cortex and elevation of the threshold of the central nervous system to convulsive stimuli.

INDICATIONS AND USAGE

Zarontin is indicated for the control of absence (petit mal) epilepsy.

CONTRAINDICATION

Ethosuximide should not be used in patients with a history of hypersensitivity to succinimides.

WARNINGS

Blood Dyscrasias:

Blood dyscrasias, including some with fatal outcome, have been reported to be associated with the use of ethosuximide; therefore, periodic blood counts should be performed. Should signs and/or symptoms of infection (e.g., sore throat, fever) develop, blood counts should be considered at that point.

Drug-induced immune thrombocytopenia (DITP) has been reported with ethosuximide. In the reported cases, the onset of symptoms occurred 1 to 3 weeks after initiation of ethosuximide; one patient had recurrence of symptoms within 1 day of a subsequent re-challenge with the drug. In those cases in which the platelet count was specified, the nadir was 2,000 and 3,000/mm^3. When DITP is suspected, discontinue Zarontin, monitor serial platelet counts, and treat as appropriate. If possible, assess the presence of drug-dependent antiplatelet antibodies. Avoid future use of Zarontin in patients with history of ethosuximide-induced DITP.

Effects on Liver and Kidneys:

Ethosuximide is capable of producing morphological and functional changes in the animal liver. In humans, abnormal liver and renal function studies have been reported. Ethosuximide should be administered with extreme caution to patients with known liver or renal disease. Periodic urinalysis and liver function studies are advised for all patients receiving the drug.

Systemic Lupus Erythematosus:

Cases of systemic lupus erythematosus have been reported with the use of ethosuximide. The physician should be alert to this possibility.

Suicidal Behavior and Ideation:

Antiepileptic drugs (AEDs), including Zarontin, increase the risk of suicidal thoughts or behavior in patients taking these drugs for any indication. Patients treated with any AED for any indication should be monitored for the emergence or worsening of depression, suicidal thoughts or behavior, and/or any unusual changes in mood or behavior.

Pooled analyses of 199 placebo-controlled clinical trials (mono- and adjunctive therapy) of 11 different AEDs showed that patients randomized to one of the AEDs had approximately twice the risk (adjusted Relative Risk 1.8, 95% CI: 1.2, 2.7) of suicidal thinking or behavior compared to patients randomized to placebo. In these trials, which had a median treatment duration of 12 weeks, the estimated incidence rate of suicidal behavior or ideation among 27,863 AED-treated patients was 0.43%, compared to 0.24% among 16,029 placebo-treated patients, representing an increase of approximately one case of suicidal thinking or behavior for every 530 patients treated. There were four suicides in drug-treated patients in the trials and none in placebo-treated patients, but the number is too small to allow any conclusion about drug effect on suicide.

The increased risk of suicidal thoughts or behavior with AEDs was observed as early as one week after starting drug treatment with AEDs and persisted for the duration of treatment assessed. Because most trials included in the analysis did not extend beyond 24 weeks, the risk of suicidal thoughts or behavior beyond 24 weeks could not be assessed.

The risk of suicidal thoughts or behavior was generally consistent among drugs in the data analyzed. The finding of increased risk with AEDs of varying mechanisms of action and across a range of indications suggests that the risk applies to all AEDs used for any indication. The risk did not vary substantially by age (5–100 years) in the clinical trials analyzed.

Table 1 shows absolute and relative risk by indication for all evaluated AEDs.

Table 1 Risk by indication for antiepileptic drugs in the pooled analysis
Indication | Placebo Patients with Events Per 1000 Patients | Drug Patients with Events Per 1000 Patients | Relative Risk: Incidence of Events in Drug Patients/Incidence in Placebo Patients | Risk Difference: Additional Drug Patients with Events Per 1000 Patients
Epilepsy | 1.0 | 3.4 | 3.5 | 2.4
Psychiatric | 5.7 | 8.5 | 1.5 | 2.9
Other | 1.0 | 1.8 | 1.9 | 0.9
Total | 2.4 | 4.3 | 1.8 | 1.9

The relative risk for suicidal thoughts or behavior was higher in clinical trials for epilepsy than in clinical trials for psychiatric or other conditions, but the absolute risk differences were similar for the epilepsy and psychiatric indications.

Anyone considering prescribing Zarontin or any other AED must balance the risk of suicidal thoughts and behavior with the risk of untreated illness. Epilepsy and many other illnesses for which AEDs are prescribed are themselves associated with morbidity and mortality and an increased risk of suicidal thoughts and behavior. Should suicidal thoughts and behavior emerge during treatment, the prescriber needs to consider whether the emergence of these symptoms in any given patient may be related to the illness being treated.

Patients, their caregivers, and families should be informed that AEDs increase the risk of suicidal thoughts and behavior and should be advised of the need to be alert for the emergence or worsening of the signs and symptoms of depression, any unusual changes in mood or behavior, or the emergence of suicidal thoughts, behavior, or thoughts about self-harm. Behaviors of concern should be reported immediately to healthcare providers.

Serious dermatologic reactions, including Stevens-Johnson syndrome (SJS), have been reported with ethosuximide treatment. SJS can be fatal. The onset of symptoms is usually within 28 days, but can occur later. Zarontin should be discontinued at the first sign of a rash, unless the rash is clearly not drug-related. If signs or symptoms suggest SJS, use of this drug should not be resumed and alternative therapy should be considered.

Drug Reaction with Eosinophilia and Systemic Symptoms (DRESS), also known as multi organ hypersensitivity, has occurred with Zarontin. Some of these events have been fatal or life-threatening. DRESS typically, although not exclusively, presents with fever, rash, lymphadenopathy and/or facial swelling, in association with other organ system involvement, such as hepatitis, nephritis, hematologic abnormalities, myocarditis, or myositis, sometimes resembling an acute viral infection. Eosinophilia is often present. This disorder is variable in its expression, and other organ systems not noted here may be involved. It is important to note that early manifestations of hypersensitivity (e.g. fever, lymphadenopathy) may be present even though rash is not evident. If such signs or symptoms are present, the patient should be evaluated immediately. Zarontin should be discontinued if an alternative etiology for the signs or symptoms cannot be established.

Usage in Pregnancy:

Ethosuximide crosses the placenta.

Reports suggest an association between the use of anticonvulsant drugs by women with epilepsy and an elevated incidence of birth defects in children born to these women. Data are more extensive with respect to phenytoin and phenobarbital, but these are also the most commonly prescribed anticonvulsants; less systematic or anecdotal reports suggest a possible similar association with the use of all known anticonvulsant drugs.

Cases of birth defects have been reported with ethosuximide. The reports suggesting an elevated incidence of birth defects in children of drug-treated epileptic women cannot be regarded as adequate to prove a definite cause and effect relationship. There are intrinsic methodological problems in obtaining adequate data on drug teratogenicity in humans; the possibility also exists that other factors, e.g., genetic factors or the epileptic condition itself, may be more important than drug therapy in leading to birth defects. The great majority of mothers on anticonvulsant medication deliver normal infants. It is important to note that anticonvulsant drugs should not be discontinued in patients in whom the drug is administered to prevent major seizures because of the strong possibility of precipitating status epilepticus with attendant hypoxia and threat to life. In individual cases where the severity and frequency of the seizure disorder are such that the removal of medication does not pose a serious threat to the patient, discontinuation of the drug may be considered prior to and during pregnancy, although it cannot be said with any confidence that even minor seizures do not pose some hazard to the developing embryo or fetus.

The prescribing physician will wish to weigh these considerations in treating or counseling epileptic women of childbearing potential.

Ethosuximide is excreted in human breast milk. Because the effects of ethosuximide on the nursing infant are unknown, caution should be exercised when ethosuximide is administered to a nursing mother. Ethosuximide should be used in nursing mothers only if the benefits clearly outweigh the risks.

PRECAUTIONS

General:

Ethosuximide, when used alone in mixed types of epilepsy, may increase the frequency of grand mal seizures in some patients.

As with other anticonvulsants, it is important to proceed slowly when increasing or decreasing dosage, as well as when adding or eliminating other medication. Abrupt withdrawal of anticonvulsant medication may precipitate absence (petit mal) status.

Information for Patients:

Inform patients of the availability of a Medication Guide, and instruct them to read the Medication Guide prior to taking Zarontin. Instruct patients to take Zarontin only as prescribed.

Ethosuximide may impair the mental and/or physical abilities required for the performance of potentially hazardous tasks, such as driving a motor vehicle or other such activity requiring alertness; therefore, the patient should be cautioned accordingly.

Patients taking ethosuximide should be advised of the importance of adhering strictly to the prescribed dosage regimen.

Patients should be instructed to promptly contact their physician if they develop signs and/or symptoms (e.g., sore throat, fever), suggesting an infection.

Patients, their caregivers, and families should be counseled that AEDs, including Zarontin, may increase the risk of suicidal thoughts and behavior and should be advised of the need to be alert for the emergence or worsening of symptoms of depression, any unusual changes in mood or behavior, or the emergence of suicidal thoughts, behavior, or thoughts about self-harm. Behaviors of concern should be reported immediately to healthcare providers.

Prior to initiation of treatment with Zarontin, the patient should be instructed that a rash may herald a serious medical event and that the patient should report any such occurrence to a physician immediately.

Patients should be encouraged to enroll in the North American Antiepileptic Drug (NAAED) Pregnancy Registry if they become pregnant. This registry is collecting information about the safety of antiepileptic drugs during pregnancy. To enroll, patients can call the toll free number 1-888-233-2334 (see PRECAUTIONS: Pregnancy section).

Drug Interactions:

Since Zarontin (ethosuximide) may interact with concurrently administered antiepileptic drugs, periodic serum level determinations of these drugs may be necessary (e.g., ethosuximide may elevate phenytoin serum levels and valproic acid has been reported to both increase and decrease ethosuximide levels).

Pregnancy:

To provide information regarding the effects of in utero exposure to Zarontin, physicians are advised to recommend that pregnant patients taking Zarontin enroll in the NAAED Pregnancy Registry. This can be done by calling the toll free number 1-888-233-2334, and must be done by patients themselves. Information on the registry can also be found at the website: http://www.aedpregnancyregistry.org/

See WARNINGS.

Pediatric Use:

Safety and effectiveness in pediatric patients below the age of 3 years have not been established. (See DOSAGE AND ADMINISTRATION section.)

ADVERSE REACTIONS

Body As A Whole: Allergic reaction, Drug Reaction with Eosinophilia and Systemic Symptoms (DRESS).

Gastrointestinal System: Gastrointestinal symptoms occur frequently and include anorexia, vague gastric upset, nausea and vomiting, cramps, epigastric and abdominal pain, weight loss, and diarrhea. There have been reports of gum hypertrophy and swelling of the tongue.

Hemopoietic System: Hemopoietic complications associated with the administration of ethosuximide have included leukopenia, agranulocytosis, pancytopenia, with or without bone marrow suppression, eosinophilia, and thrombocytopenia (see WARNINGS).

Nervous System: Neurologic and sensory reactions reported during therapy with ethosuximide have included drowsiness, headache, dizziness, euphoria, hiccups, irritability, hyperactivity, lethargy, fatigue, and ataxia. Psychiatric or psychological aberrations associated with ethosuximide administration have included disturbances of sleep, night terrors, inability to concentrate, and aggressiveness. These effects may be noted particularly in patients who have previously exhibited psychological abnormalities. There have been rare reports of paranoid psychosis, increased libido, and increased state of depression with overt suicidal intentions.

Integumentary System: Dermatologic manifestations which have occurred with the administration of ethosuximide have included urticaria, pruritic erythematous rashes, Stevens-Johnson syndrome, and hirsutism.

Special Senses: Myopia.

Genitourinary System: Vaginal bleeding, microscopic hematuria.

OVERDOSAGE

Acute overdoses may produce nausea, vomiting, and CNS depression including coma with respiratory depression. A relationship between ethosuximide toxicity and its plasma levels has not been established. The therapeutic range of serum levels is 40 mcg/mL to 100 mcg/mL, although levels as high as 150 mcg/mL have been reported without signs of toxicity.

Treatment:

Treatment should include emesis (unless the patient is or could rapidly become obtunded, comatose, or convulsing) or gastric lavage, activated charcoal, cathartics, and general supportive measures. Hemodialysis may be useful to treat ethosuximide overdose. Forced diuresis and exchange transfusions are ineffective.

DOSAGE AND ADMINISTRATION

Zarontin is administered by the oral route. The initial dose for patients 3 to 6 years of age is one capsule (250 mg) per day; for patients 6 years of age and older, 2 capsules (500 mg) per day. The dose thereafter must be individualized according to the patient's response. Dosage should be increased by small increments. One useful method is to increase the daily dose by 250 mg every four to seven days until control is achieved with minimal side effects. Dosages exceeding 1.5 g daily, in divided doses, should be administered only under the strictest supervision of the physician. The optimal dose for most pediatric patients is 20 mg/kg/day. This dose has given average plasma levels within the accepted therapeutic range of 40 to 100 mcg/mL. Subsequent dose schedules can be based on effectiveness and plasma level determinations.

Zarontin may be administered in combination with other anticonvulsants when other forms of epilepsy coexist with absence (petit mal). The optimal dose for most pediatric patients is 20 mg/kg/day.

HOW SUPPLIED

Zarontin is supplied as:

NDC 0071-0237-24: Bottles of 100. Each capsule contains 250 mg ethosuximide.

STORAGE AND HANDLING

Store at 25° C (77° F); excursions permitted to 15–30° C (59–86° F) [see USP Controlled Room Temperature].

LAB-0094-12.0

Revised June 2023

MEDICATION GUIDE ZARONTIN, (Ză rŏn' tĭn) (ethosuximide) Capsules, Oral Solution

Read this Medication Guide before you start taking ZARONTIN and each time you get a refill. There may be new information. This information does not take the place of talking to your healthcare provider about your medical condition or treatment. If you have any questions about ZARONTIN, ask your healthcare provider or pharmacist.

What is the most important information I should know about ZARONTIN?

Do not stop taking ZARONTIN without first talking to your healthcare provider.
Stopping ZARONTIN suddenly can cause serious problems.

ZARONTIN can cause serious side effects, including:

1. Rare but serious blood problems that may be life-threatening. Call your healthcare provider right away if you have:
  1. fever, swollen glands, or sore throat that come and go or do not go away
  2. frequent infections or an infection that does not go away
  3. easy bruising
  4. red or purple spots on your body
  5. bleeding gums or nose bleeds
  6. severe fatigue or weakness
2. Drug reactions that may affect different parts of the body such as your liver, kidneys, heart, or blood cells. You may or may not have a rash with these types of reactions. These reactions can be very serious and can cause death. Call your healthcare provider right away if you have any of these symptoms:
  1. joint pain and swelling
  2. muscle pain
  3. fatigue, weakness
  4. low-grade fever
  5. pain in the chest that is worse with breathing
  6. skin rash
  7. swollen lymph glands
  8. swelling of your face
  9. yellowing of your skin or the white part of your eyes
3. Like other antiepileptic drugs, ZARONTIN may cause suicidal thoughts or actions in a very small number of people, about 1 in 500.
  Call a healthcare provider right away if you have any of these symptoms, especially if they are new, worse, or worry you:
  1. thoughts about suicide or dying
  2. attempts to commit suicide
  3. new or worse depression
  4. new or worse anxiety
  5. feeling agitated or restless
  6. panic attacks
  7. trouble sleeping (insomnia)
  8. new or worse irritability
  9. acting aggressive, being angry, or violent
  10. acting on dangerous impulses
  11. an extreme increase in activity and talking (mania)
  12. other unusual changes in behavior or mood
How can I watch for early symptoms of suicidal thoughts and actions?
  1. Pay attention to any changes, especially sudden changes, in mood, behaviors, thoughts, or feelings.
  2. Keep all follow-up visits with your healthcare provider as scheduled.
Call your healthcare provider between visits as needed, especially if you are worried about symptoms.
Do not stop ZARONTIN without first talking to a healthcare provider.
  1. Stopping ZARONTIN suddenly can cause serious problems.
  2. Stopping a seizure medicine suddenly in a patient who has epilepsy can cause seizures that will not stop (status epilepticus).
Suicidal thoughts or actions can be caused by things other than medicines. If you have suicidal thoughts or actions, your healthcare provider may check for other causes.

What is ZARONTIN?

ZARONTIN is a prescription medicine used to treat absence (petit mal) seizures.

Who should not take ZARONTIN?

Do not take ZARONTIN if you are allergic to succinimides (methsuximide or ethosuximide), or any of the ingredients in ZARONTIN. See the end of this Medication Guide for a complete list of ingredients in ZARONTIN.

What should I tell my healthcare provider before taking ZARONTIN?

Before you take ZARONTIN, tell your healthcare provider if you:

- have or had liver problems
- have or have had depression, mood problems or suicidal thoughts or behavior
- have any other medical conditions
- are pregnant or plan to become pregnant. It is not known if ZARONTIN can harm your unborn baby. Tell your healthcare provider right away if you become pregnant while taking ZARONTIN. You and your healthcare provider should decide if you should take ZARONTIN while you are pregnant.
  - If you become pregnant while taking ZARONTIN, talk to your healthcare provider about registering with the North American Antiepileptic Drug (NAAED) Pregnancy Registry. The purpose of this registry is to collect information about the safety of antiepileptic drugs during pregnancy. You can enroll in this registry by calling 1-888-233-2334.
- are breast-feeding or plan to breast-feed. It is not known if ZARONTIN can pass into breast milk. You and your healthcare provider should decide how you will feed your baby while you take ZARONTIN.

Tell your healthcare provider about all the medicines you take, including prescription and non-prescription medicines, vitamins, and herbal supplements. Taking ZARONTIN with certain other medicines can cause side effects or affect how well they work. Do not start or stop other medicines without talking to your healthcare provider.

Know the medicines you take. Keep a list of them with you to show your healthcare provider and pharmacist when you get a new medicine.

How should I take ZARONTIN?

- Take ZARONTIN exactly as prescribed. Your healthcare provider will tell you how much ZARONTIN to take.
- Your healthcare provider may change your dose. Do not change your dose of ZARONTIN without talking to your healthcare provider.
- If you take too much ZARONTIN, call your healthcare provider or your local Poison Control Center right away.

What should I avoid while taking ZARONTIN?

- Do not drink alcohol or take other medicines that make you sleepy or dizzy while taking ZARONTIN without first talking to your healthcare provider. ZARONTIN taken with alcohol or medicines that cause sleepiness or dizziness may make your sleepiness or dizziness worse.
  - Do not drive, operate heavy machinery, or do other dangerous activities until you know how ZARONTIN affects you. ZARONTIN can slow your thinking and motor skills.

What are the possible side effects of ZARONTIN?

- See "What is the most important information I should know about ZARONTIN?"

ZARONTIN may cause other serious side effects, including:

- Serious allergic reactions. Call your healthcare provider right away if you have any of these symptoms:
  - skin rash
  - hives
  - sores in your mouth
  - blistering or peeling skin
- Changes in thinking, mood, or behavior. Some patients may get abnormally suspicious thoughts, hallucinations (seeing or hearing things that are not there), or delusions (false thoughts or beliefs).
- Grand mal seizures can happen more often or become worse

Call your healthcare provider right away, if you have any of the symptoms listed above.

The most common side effects of ZARONTIN include

- nausea or vomiting
- indigestion, stomach pain
- diarrhea
- weight loss
- loss of appetite
- hiccups

- fatigue
- dizziness or lightheadedness
- unsteadiness when walking
- headache
- loss of concentration

Tell your healthcare provider about any side effect that bothers you or that does not go away.

These are not all the possible side effects with ZARONTIN. For more information, ask your healthcare provider or pharmacist.

Call your doctor for medical advice about side effects. You may report side effects to FDA at 1-800-FDA-1088.

How should I store ZARONTIN?

- Store ZARONTIN capsules at room temperature, between 59°F to 86°F (15°C to 30°C).
- Store ZARONTIN syrup (oral solution) at 20°–25°C (68°–77°F). Preserve in tight containers. Protect from freezing and light.

Keep ZARONTIN and all medicines out of the reach of children.

General information about ZARONTIN

Medicines are sometimes prescribed for purposes other than those listed in a Medication Guide. Do not use ZARONTIN for a condition for which it was not prescribed. Do not give ZARONTIN to other people, even if they have the same condition. It may harm them.

This Medication Guide summarizes the most important information about ZARONTIN. If you would like more information, talk with your healthcare provider. You can ask your healthcare provider or pharmacist for information about ZARONTIN that is written for healthcare professionals.

For more information, go to www.pfizer.com or call 1-800-438-1985.

What are the ingredients in ZARONTIN?

Active ingredient: ethosuximide

Capsules
Inactive ingredients: Polyethylene glycol 400, NF; D&C yellow No. 10; FD&C red No. 3; gelatin, NF; glycerin, USP; and sorbitol.

Oral Solution
Inactive ingredients: Each 5 ml (teaspoonful) of oral solution contains 250 mg ethosuximide in a raspberry flavored base. Also contains citric acid, anhydrous, USP; FD&C red No. 40; FD&C yellow No. 6; flavor; glycerin, USP; purified water, USP; saccharin sodium, USP; sodium benzoate, NF; Sodium Citrate, USP; sucrose, NF.

This Medication Guide has been approved by the U.S. Food and Drug Administration.

LAB-0403-4.0

June 2023

PRINCIPAL DISPLAY PANEL - 250 mg Capsule Bottle Label

ALWAYS DISPENSE WITH
ACCOMPANYING MEDICATION GUIDE

NDC 0071-0237-24

Pfizer

Zarontin®
(ethosuximide
capsules, USP)

250 mg

100 Capsules
Rx only